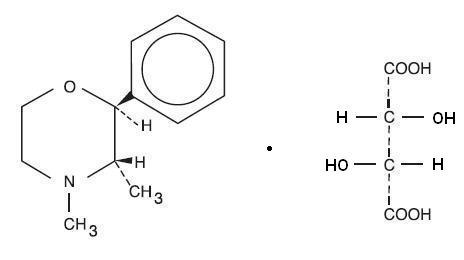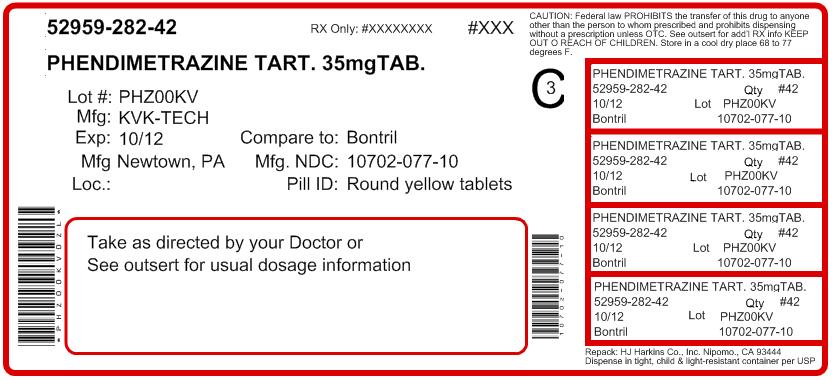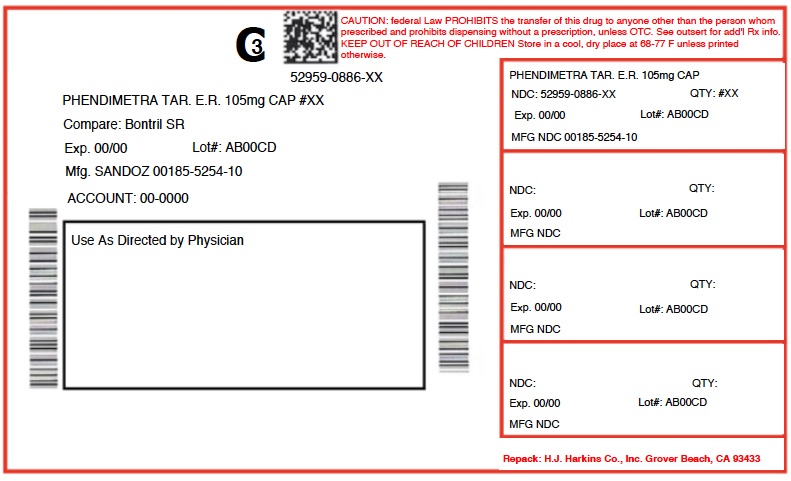 DRUG LABEL: PHENDIMETRAZINE TARTRATE
NDC: 52959-886 | Form: CAPSULE, EXTENDED RELEASE
Manufacturer: H.J. Harkins Company, Inc.
Category: prescription | Type: HUMAN PRESCRIPTION DRUG LABEL
Date: 20180921
DEA Schedule: CIII

ACTIVE INGREDIENTS: PHENDIMETRAZINE TARTRATE 105 mg/1 1

0282/0886 PHENDIMETRAZINE

DESCRIPTION

Phendimetrazine tartrate, as the dextro isomer, has the chemical name of (2S,3S)-3,4-Dimethyl-2-phenylmorpholine L-(+)- tartrate (1:1).

The structural formula is:

Phendimetrazine tartrate is a white, odorless crystalline powder. It is freely soluble in water; sparingly soluble in warm alcohol, insoluble in chloroform, acetone, ether and benzene.

Each white tablet, for oral administration, contains 35 mg of phendimetrazine tartrate. In addition, the following inactive ingredients are present: Colloidal Silicon Dioxide, Lactose Monohydrate, Magnesium Stearate, Microcrystalline Cellulose 102 and Sodium Starch Glycolate. The yellow tablet also contains FD&C Yellow # 5 Aluminum Lake (15-17%). The blue tablet also contains FD&C Blue # 1 Aluminum Lake (11-13%).

CLINICAL PHARMACOLOGY

Phendimetrazine tartrate is a sympathomimetic amine with pharmacological activity similar to the prototype drugs of this class used in obesity, the amphetamines. Actions include central nervous system stimulation and elevation of blood pressure. Tachyphylaxis and tolerance have been demonstrated with all drugs of this class in which these phenomena have been looked for.

Drugs of this class used in obesity are commonly known as “anorectics” or “anorexigenics”. It has not been established, however, that the action of such drugs in treating obesity is primarily one of appetite suppression. Other central nervous system actions or metabolic effects, may be involved for example.

Adult obese subjects instructed in dietary management and treated with anorectic drugs, lose more weight on the average than those treated with placebo and diet, as determined in relatively short term clinical trials.

The magnitude of increased weight loss of drug-treated patients over placebo-treated patients is only a fraction of a pound a week. The rate of weight loss is greatest in the first weeks of therapy for both drug and placebo subjects and tends to decrease in succeeding weeks. The possible origin of the increased weight loss due to the various drug effects is not established. The amount of weight loss associated with the use of an anorectic drug varies from trial to trial, and the increased weight loss appears to be related in part to variables other than the drug prescribed, such as the physician investigator, the population treated, and the diet prescribed. Studies do not permit conclusions as to the relative importance of the drug and non-drug factors on weight loss.

The natural history of obesity is measured in years, whereas the studies cited are restricted to a few weeks duration; thus, the total impact of drug-induced weight loss over that of diet alone must be considered clinically limited.

The major route of elimination is via the kidneys where most of the drug and metabolites are excreted. Some of the drug is metabolized to phendimetrazine and phendimetrazine-N-oxide. The average half-life of elimination when studied under controlled conditions is about 3.7 hours for both the extended-release and immediate release forms. The absorption half-life of the drug from the immediate release 35 mg phendimetrazine tablets is appreciably more rapid than the absorption rate of the drug from the extended-release formulation.

INDICATIONS AND USAGE

Phendimetrazine tartrate is indicated in the management of exogenous obesity as a short term adjunct (a few weeks) in a regimen of weight reduction based on caloric restriction in patients with an initial body mass index (BMI) of 30 kg/m^2 or higher who have not responded to appropriate weight reducing regimen (diet and/or exercise) alone. Below is a chart of Body Mass Index (BMI) based on various heights and weights. BMI is calculated by taking the patient’s weight, in kilograms (kg), divided by the patient’s height, in meters (m), squared. Metric conversions are as follows: pounds ÷ 2.2 = kg; inches x 0.0254 = meters.

BODY MASS INDEX (BMI), kg/m^2 Height (feet, inches)
Weight(pounds) | 5’0” | 5’3” | 5’6” | 5’9” | 6’0” | 6’3”
140 | 27 | 25 | 23 | 21 | 19 | 18
150 | 29 | 27 | 24 | 22 | 20 | 19
160 | 31 | 28 | 26 | 24 | 22 | 20
170 | 33 | 30 | 28 | 25 | 23 | 21
180 | 35 | 32 | 29 | 27 | 25 | 23
190 | 37 | 34 | 31 | 28 | 26 | 24
200 | 39 | 36 | 32 | 30 | 27 | 25
210 | 41 | 37 | 34 | 31 | 29 | 26
220 | 43 | 39 | 36 | 33 | 30 | 28
230 | 45 | 41 | 37 | 34 | 31 | 29
240 | 47 | 43 | 39 | 36 | 33 | 30
250 | 49 | 44 | 40 | 37 | 34 | 31

Phendimetrazine tartrate is indicated for use as monotherapy only.

CONTRAINDICATIONS

Known hypersensitivity or idiosyncratic reactions to sympathomimetics.

Advanced arteriosclerosis, symptomatic cardiovascular disease, moderate and severe hypertension, hyperthyroidism, and glaucoma.

Highly nervous or agitated patients.

Patients with a history of drug abuse.

Patients taking other CNS stimulants, including monoamine oxidase inhibitors.

WARNINGS

Phendimetrazine tartrate should not be used in combination with other anorectic agents, including prescribed drugs, over-the-counter preparations and herbal products.

In a case-control epidemiological study, the use of anorectic agents, including phendimetrazine tartrate, was associated with an increased risk of developing pulmonary hypertension, a rare, but often fatal disorder. The use of anorectic agents for longer than three months was associated with a 23-fold increase in the risk of developing pulmonary hypertension. Increased risk of pulmonary hypertension with repeated courses of therapy cannot be excluded.

The onset or aggravation of exertional dyspnea, or unexplained symptoms of angina pectoris, syncope, or lower extremity edema suggest the possibility of occurrence of pulmonary hypertension. Under these circumstances, phendimetrazine tartrate should be immediately discontinued, and the patient should be evaluated for the possible presence of pulmonary hypertension.

Valvular heart disease associated with the use of some anorectic agents such as fenfluramine and dexfenfluramine has been reported. Possible contributing factors include use for extended periods of time, higher than recommended dose, and/or use in combination with other anorectic drugs. However, no cases of this valvulopathy have been reported when phendimetrazine tartrate has been used alone.

The potential risk of possible serious adverse effects such as valvular heart disease and pulmonary hypertension should be assessed carefully against the potential benefit of weight loss. Baseline cardiac evaluation should be considered to detect pre-existing valvular heart diseases or pulmonary hypertension prior to initiation of phendimetrazine treatment. Phendimetrazine tartrate is not recommended in patients with known heart murmur or valvular heart disease. Echocardiogram during and after treatment could be useful for detecting any valvular disorders which may occur. To limit unwarranted exposure and risks, treatment with phendimetrazine tartrate should be continued only if the patient has satisfactory weight loss within the first 4 weeks of treatment (i.e., weight loss of at least 4 pounds, or as determined by the physician and patient).

Tolerance to the anorectic effect of phendimetrazine develops within a few weeks. When this occurs, its use should be discontinued; the maximum recommended dose should not be exceeded.

Use of phendimetrazine tartrate within 14 days following the administration of monoamine oxidase inhibitors may result in a hypertensive crisis.

Abrupt cessation of administration following prolonged high dosage results in extreme fatigue and depression. Because of the effect on the central nervous system, phendimetrazine tartrate may impair the ability of the patient to engage in potentially hazardous activities such as operating machinery or driving a motor vehicle; the patient should therefore be cautioned accordingly.

Phendimetrazine tartrate is not recommended for patients who used any anorectic agents within the prior year.

PRECAUTIONS

Caution is to be exercised in prescribing phendimetrazine for patients with even mild hypertension.

Insulin requirements in diabetes mellitus may be altered in association with the use of phendimetrazine tartrate and the concomitant dietary regimen.

Phendimetrazine tartrate may decrease the hypotensive effect of guanethidine. The least amount feasible should be prescribed or dispensed at one time in order to minimize the possibility of overdosage.

Only yellow tablet contains FD&C Yellow No. 5 (tartrazine) which may cause allergic-type reactions (including bronchial asthma) in certain susceptible persons. Although the overall incidence of FD&C Yellow No. 5 (tartrazine) sensitivity in the general population is low, it is frequently seen in patients who also have aspirin hypersensitivity.

Drug Interactions:

Efficacy of phendimetrazine tartrate with other anorectic agents has not been studied and the combined use may have the potential for serious cardiac problems.

Carcinogenesis, Mutagenesis, Impairment of Fertility:

Studies with Phendimetrazine Tartrate have not been performed to evaluate carcinogenic potential, mutagenic potential or effects on fertility.

Pregnancy: Pregnancy Category C:

Animal reproduction studies have not been conducted with phendimetrazine tartrate. It is also not known whether phendimetrazine tartrate can cause fetal harm when administered to a pregnant woman or can affect reproduction capacity.

Usage in Pregnancy:

Safe use in pregnancy has not been established. Until more information is available, phendimetrazine tartrate should not be taken by women who are or may become pregnant unless, in the opinion of the physician, the potential benefits outweigh the possible hazards.

Nursing Mothers:

It is not known whether this drug is excreted in human milk. Because many drugs are excreted in human milk, phendimetrazine tartrate should not be taken by women who are nursing unless, in the opinion of the physician, the potential benefits outweigh the possible hazards.

Pediatric Use:

Safety and effectiveness in pediatric patients have not been established.

ADVERSE REACTIONS:

Cardiovascular: Palpitations, tachycardia, elevated blood pressure, ischemic events.

Valvular heart disease associated with the use of some anorectic agents such as fenfluramine and dexfenfluramine, both independently and especially when used in combination with other anorectic drugs, have been reported. However, no case of this valvulopathy has been reported when phendimetrazine tartrate has been used alone.

Central Nervous System:

Overstimulation, restlessness, insomnia, agitation, flushing, tremor, sweating, dizziness, headache, psychotic state, blurring of vision.

Gastrointestinal:

Dryness of the mouth, nausea, diarrhea, constipation, stomach pain.

Genitourinary:

Urinary frequency, dysuria, changes in libido.

DRUG ABUSE AND DEPENDENCE:

Controlled Substance:

Phendimetrazine tartrate tablets are a Schedule lll controlled substance.

Dependence:

Phendimetrazine tartrate is related chemically and pharmacologically to the amphetamines. Amphetamines and related stimulant drugs have been extensively abused, and the possibility of abuse of phendimetrazine should be kept in mind when evaluating the desirability of including a drug as part of a weight reduction program. Abuse of amphetamines and related drugs may be associated with intense psychological dependence and severe social dysfunction. There are reports of patients who have increased the dosage to many times that recommended. Abrupt cessation following prolonged high dosage administration results in extreme fatigue and mental depression; changes are also noted on the sleep EEG. Manifestations of chronic intoxication with anorectic drugs include severe dermatoses, marked insomnia, irritability, hyperactivity and personality changes. The most severe manifestation of chronic intoxications is psychosis, often clinically indistinguishable from schizophrenia.

OVERDOSAGE:

Acute overdosage with phendimetrazine tartrate may manifest itself by the following signs and symptoms: unusual restlessness, confusion, belligerence, hallucinations, and panic states. Fatigue and depression usually follow the central stimulation. Cardiovascular effects include arrhythmias, hypertension, or hypotension and circulatory collapse. Gastrointestinal symptoms include nausea, vomiting, diarrhea, and abdominal cramps. Poisoning may result in convulsions, coma, and death.

The management of overdosage is largely symptomatic. It includes sedation with a barbiturate. If hypertension is marked, the use of a nitrate or rapid-acting alpha receptor-blocking agent should be considered. Experience with hemodialysis or peritoneal dialysis is inadequate to permit recommendations for its use.

DOSAGE AND ADMINISTRATION

Dosage should be individualized to obtain an adequate response with the lowest effective dosage.

Store at 20° to 25°C (68° to 77°F); excursions permitted between 15° to 30°C (59° to 86°F)